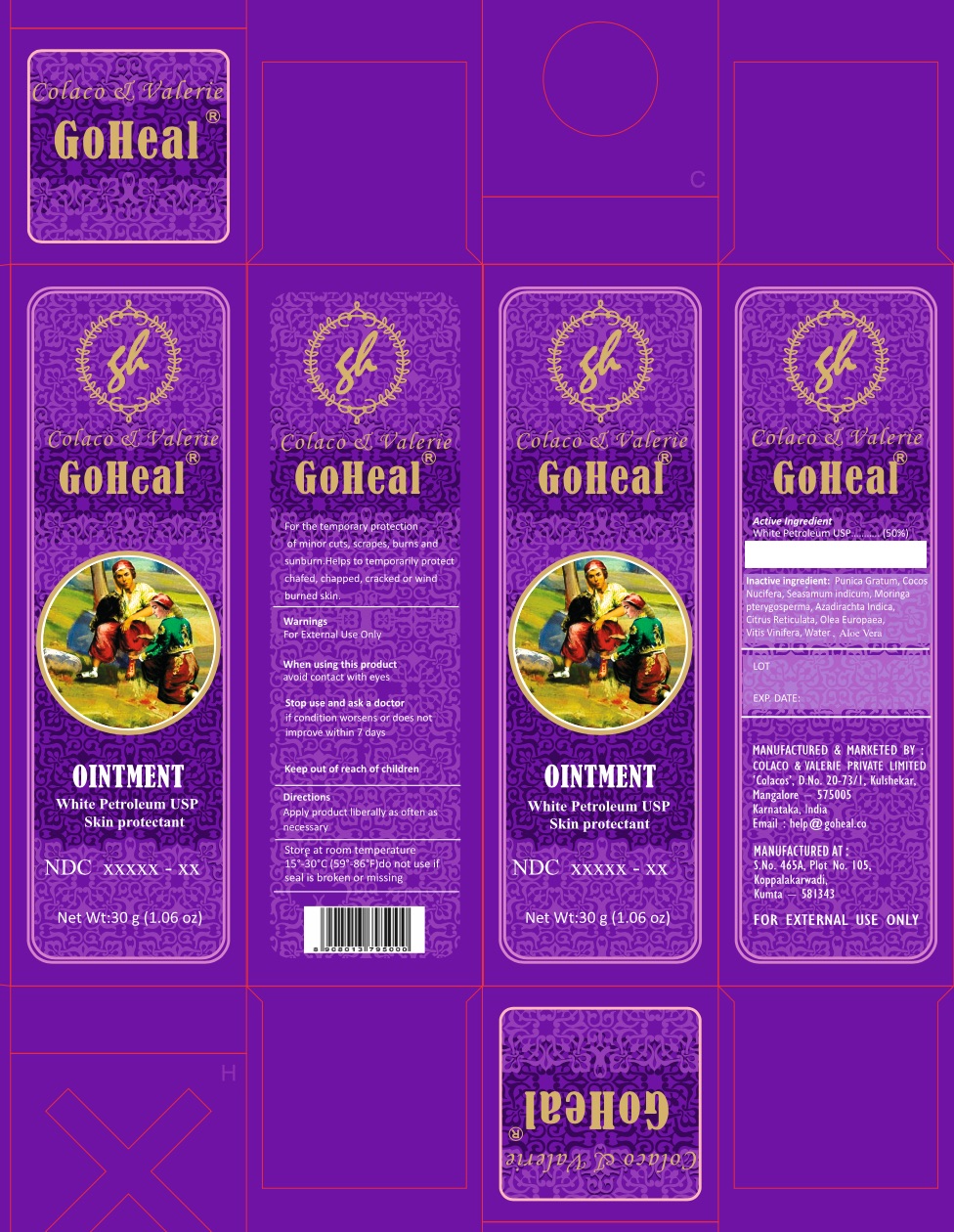 DRUG LABEL: GoHeal
NDC: 81928-002 | Form: OINTMENT
Manufacturer: Adapted Living Solutions Inc.
Category: otc | Type: HUMAN OTC DRUG LABEL
Date: 20221220

ACTIVE INGREDIENTS: PETROLATUM 15 g/30 g
INACTIVE INGREDIENTS: PUNICA GRANATUM SEED OIL; SESAME OIL; AZADIRACHTA INDICA LEAF; WATER; MORINGA OLEIFERA SEED OIL; CITRUS RETICULATA FRUIT OIL; OLEA EUROPAEA (OLIVE) OIL UNSAPONIFIABLES; ALOE VERA LEAF

GoHeal Ointment

Active Ingredient

White Petrolatum USP (50%)

Purpose

Skin protectant

Uses

- For the temporary protection of minor cuts, scrapes, burns and sunburn.
- Helps to temporarily protect chafed, chapped, cracked or windburned skin and lips.

Warnings

For External Use Only

Do not use

over deep or puncture wounds infections or lacerations. Ask a doctor

When using this product

avoid contact with eyes

Stop use and ask a doctor

if condition worsens or does not improve within 7 days

Keep out of reach of children

if swallowed get medical help or contact a Poison Control Center right away.

Directions

Apply product liberally as often as necessary

Inactive ingredient

Punica Granatum Seed Oil
Cocos Nucifera (Coconut) Oil
Sesamum Indicum (Sesame) Seed Oil
Neem (Azadirachta indica) leaf extract
Citrus Reticulata (Tangerine) Peel Essential Oil
Olea Europaea (Olive) Fruit Oil
Aloe Vera Leaf Extract
Moringa oleifera seed oil,

Water